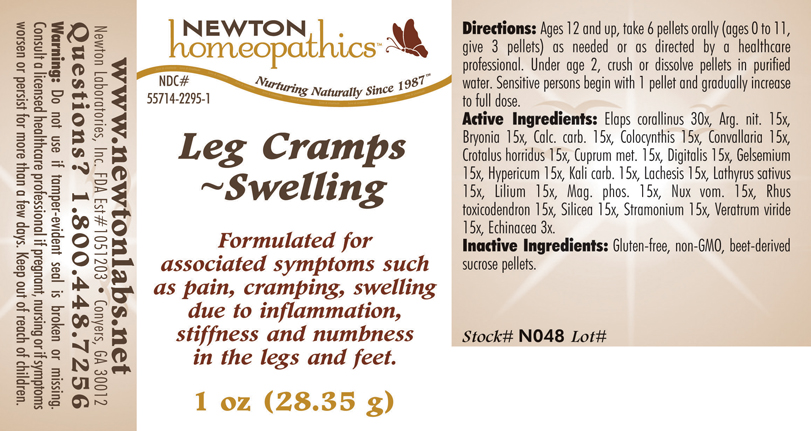 DRUG LABEL: Leg Cramps - Swelling 
NDC: 55714-2295 | Form: PELLET
Manufacturer: Newton Laboratories, Inc.
Category: homeopathic | Type: HUMAN OTC DRUG LABEL
Date: 20110301

ACTIVE INGREDIENTS: Micrurus Corallinus Venom 30 [hp_X]/1 g; Silver Nitrate 15 [hp_X]/1 g; Bryonia Alba Root 15 [hp_X]/1 g; Oyster Shell Calcium Carbonate, Crude 15 [hp_X]/1 g; Citrullus Colocynthis Fruit Pulp 15 [hp_X]/1 g; Convallaria Majalis 15 [hp_X]/1 g; Crotalus Horridus Horridus Venom 15 [hp_X]/1 g; Copper 15 [hp_X]/1 g; Digitalis 15 [hp_X]/1 g; Gelsemium Sempervirens Root 15 [hp_X]/1 g; Hypericum Perforatum 15 [hp_X]/1 g; Potassium Carbonate 15 [hp_X]/1 g; Lachesis Muta Venom 15 [hp_X]/1 g; Lathyrus Sativas Seed 15 [hp_X]/1 g; Lilium Lancifolium Whole Flowering 15 [hp_X]/1 g; Magnesium Phosphate, Dibasic Trihydrate 15 [hp_X]/1 g; Strychnos Nux-vomica Seed 15 [hp_X]/1 g; Toxicodendron Pubescens Leaf 15 [hp_X]/1 g; Silicon Dioxide 15 [hp_X]/1 g; Datura Stramonium 15 [hp_X]/1 g; Veratrum Viride Root 15 [hp_X]/1 g; Echinacea, Unspecified 3 [hp_X]/1 g
INACTIVE INGREDIENTS: Sucrose

Leg Cramps - Swelling

INDICATIONS & USAGE SECTION

Leg Cramps - Swelling Formulated for associated symptoms such as pain, cramping, swelling due to inflammation, stiffness and numbness in the legs and feet.

DOSAGE & ADMINISTRATION SECTION

Directions: Ages 12 and up, take 6 pellets orally (ages 0 to 11, give 3 pellets) as needed or as directed by a healthcare professional. Under age 2, crush or dissolve pellets in purified water. Sensitive persons begin with 1 pellet and gradually increase to full dose.

OTC - ACTIVE INGREDIENT SECTION

Elaps corallinus 30x, Arg. nit. 15x, Bryonia 15x, Calc. carb. 15x, Colocynthis 15x, Convallaria 15x, Crotalus horridus 15x, Cuprum met. 15x, Digitalis 15x, Gelsemium 15x, Hypericum 15x, Kali carb. 15x, Lachesis 15x, Lathyrus sativus 15x, Lilium 15x, Mag. phos. 15x, Nux vom. 15x, Rhus toxicodendron 15x, Silicea 15x, Stramonium 15x, Veratrum viride 15x, Echinacea 3x.

OTC - PURPOSE SECTION

Formulated for associated symptoms such as pain, cramping, swelling due to inflammation, stiffness and numbness in the legs and feet.

INACTIVE INGREDIENT SECTION

Inactive Ingredients: Gluten-free, non-GMO, beet-derived sucrose pellets.

QUESTIONS SECTION

www.newtonlabs.net Newton Laboratories, Inc. FDA Est # 1051203 - Conyers, GA 30012
Questions? 1.800.448.7256

WARNINGS SECTION

Warning: Do not use if tamper - evident seal is broken or missing. Consult a licensed healthcare professional if pregnant, nursing or if symptoms worsen or persist for more than a few days. Keep out of reach of children.

OTC - PREGNANCY OR BREAST FEEDING SECTION

Consult a licensed healthcare professional if pregnant, nursing or if symptoms worsen or persist for more than a few days.

OTC - KEEP OUT OF REACH OF CHILDREN SECTION

Keep out of reach of children.